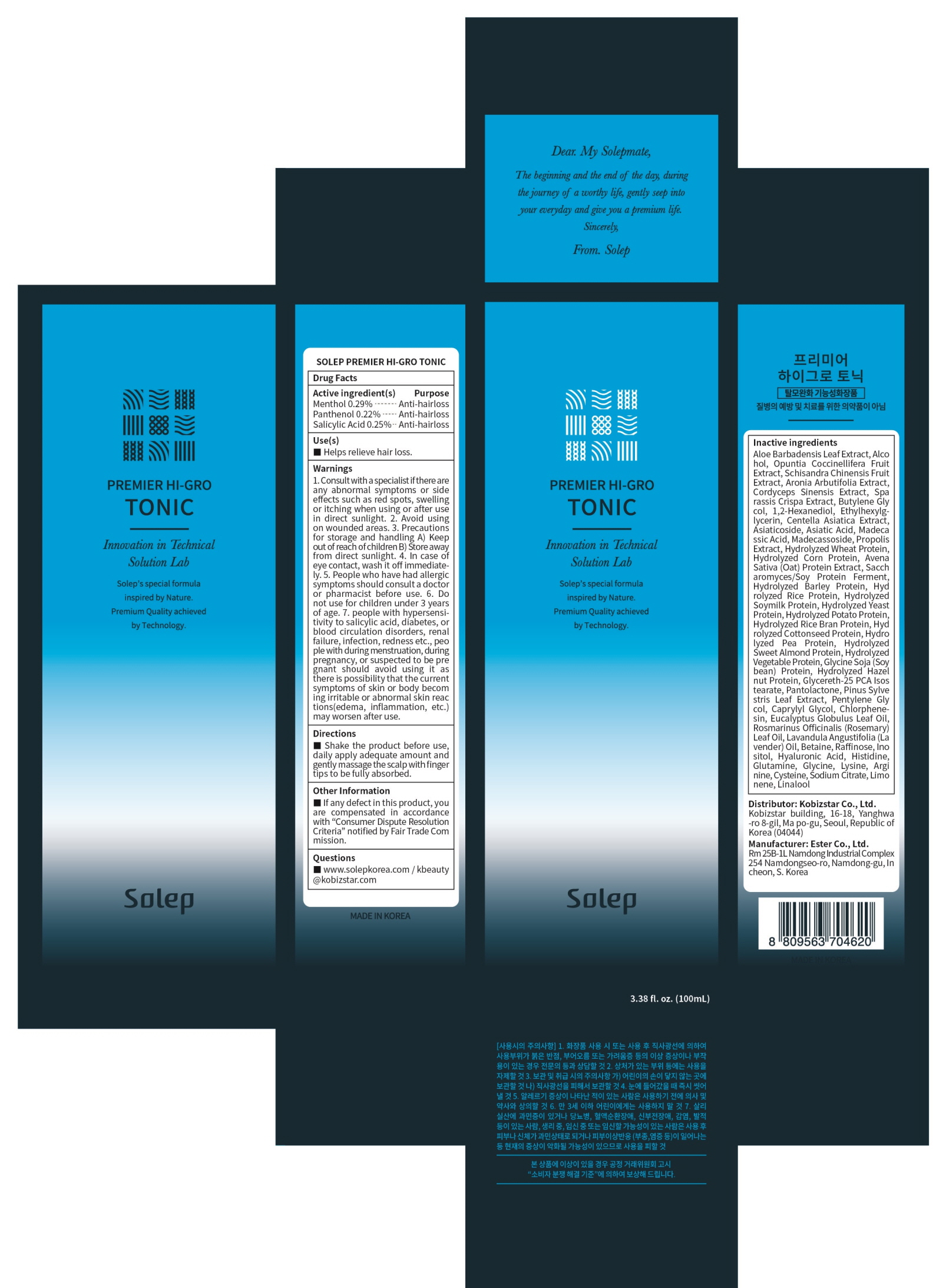 DRUG LABEL: SOLEP PREMIER HI GRO TONIC
NDC: 81077-020 | Form: SPRAY
Manufacturer: Kobizstar Co., Ltd.
Category: otc | Type: HUMAN OTC DRUG LABEL
Date: 20201117

ACTIVE INGREDIENTS: Menthol 0.29 g/100 mL; Panthenol 0.22 g/100 mL; Salicylic Acid 0.25 g/100 mL
INACTIVE INGREDIENTS: ALOE VERA LEAF; Alcohol

ACTIVE INGREDIENT(S)

Menthol 0.29%
Panthenol 0.22%
Salicylic Acid 0.25%

INACTIVE INGREDIENTS

Aloe Barbadensis Leaf Extract, Alcohol, Opuntia Coccinellifera Fruit Extract, Schisandra Chinensis Fruit Extract, Aronia Arbutifolia Extract, Cordyceps Sinensis Extract, Sparassis Crispa Extract, Butylene Glycol, 1,2-Hexanediol, Ethylhexylglycerin, Centella Asiatica Extract, Asiaticoside, Asiatic Acid, Madecassic Acid, Madecassoside, Propolis Extract, Hydrolyzed Wheat Protein, Hydrolyzed Corn Protein, Avena Sativa (Oat) Protein Extract, Saccharomyces/Soy Protein Ferment, Hydrolyzed Barley Protein, Hydrolyzed Rice Protein, Hydrolyzed Soymilk Protein, Hydrolyzed Yeast Protein, Hydrolyzed Potato Protein, Hydrolyzed Rice Bran Protein, Hydrolyzed Cottonseed Protein, Hydrolyzed Pea Protein, Hydrolyzed Sweet Almond Protein, Hydrolyzed Vegetable Protein, Glycine Soja (Soybean) Protein, Hydrolyzed Hazelnut Protein, Glycereth-25 PCA Isostearate, Pantolactone, Pinus Sylvestris Leaf Extract, Pentylene Glycol, Caprylyl Glycol, Chlorphenesin, Eucalyptus Globulus Leaf Oil, Rosmarinus Officinalis (Rosemary) Leaf Oil, Lavandula Angustifolia (Lavender) Oil, Betaine, Raffinose, Inositol, Hyaluronic Acid, Histidine, Glutamine, Glycine, Lysine, Arginine, Cysteine, Sodium Citrate, Limonene, Linalool

PURPOSE

Anti-hairloss

WARNINGS

1. Consult with a specialist if there are any abnormal symptoms or side effects such as red spots, swelling or itching when using or after use in direct sunlight. 2. Avoid using on wounded areas. 3. Precautions for storage and handling A) Keep out of reach of children B) Store away from direct sunlight. 4. In case of eye contact, wash it off immediately. 5. People who have had allergic symptoms should consult a doctor or pharmacist before use. 6. Do not use for children under 3 years of age. 7. people with hypersensitivity to salicylic acid, diabetes, or blood circulation disorders, renal failure, infection, redness etc., people with during menstruation, during pregnancy, or suspected to be pregnant should avoid using it as there is possibility that the current symptoms of skin or body becoming irritable or abnormal skin reactions(edema, inflammation, etc.) may worsen after use.

KEEP OUT OF REACH OF CHILDREN

Use(s)

■ Helps relieve hair loss.

Directions

■ Shake the product before use, daily apply adequate amount and gently massage the scalp with fingertips to be fully absorbed.

Other Information

■ If any defect in this product, you are compensated in accordance with “Consumer Dispute Resolution Criteria” notified by Fair Trade Commission.

Questions

■ www.solepkorea.com / kbeauty@kobizstar.com